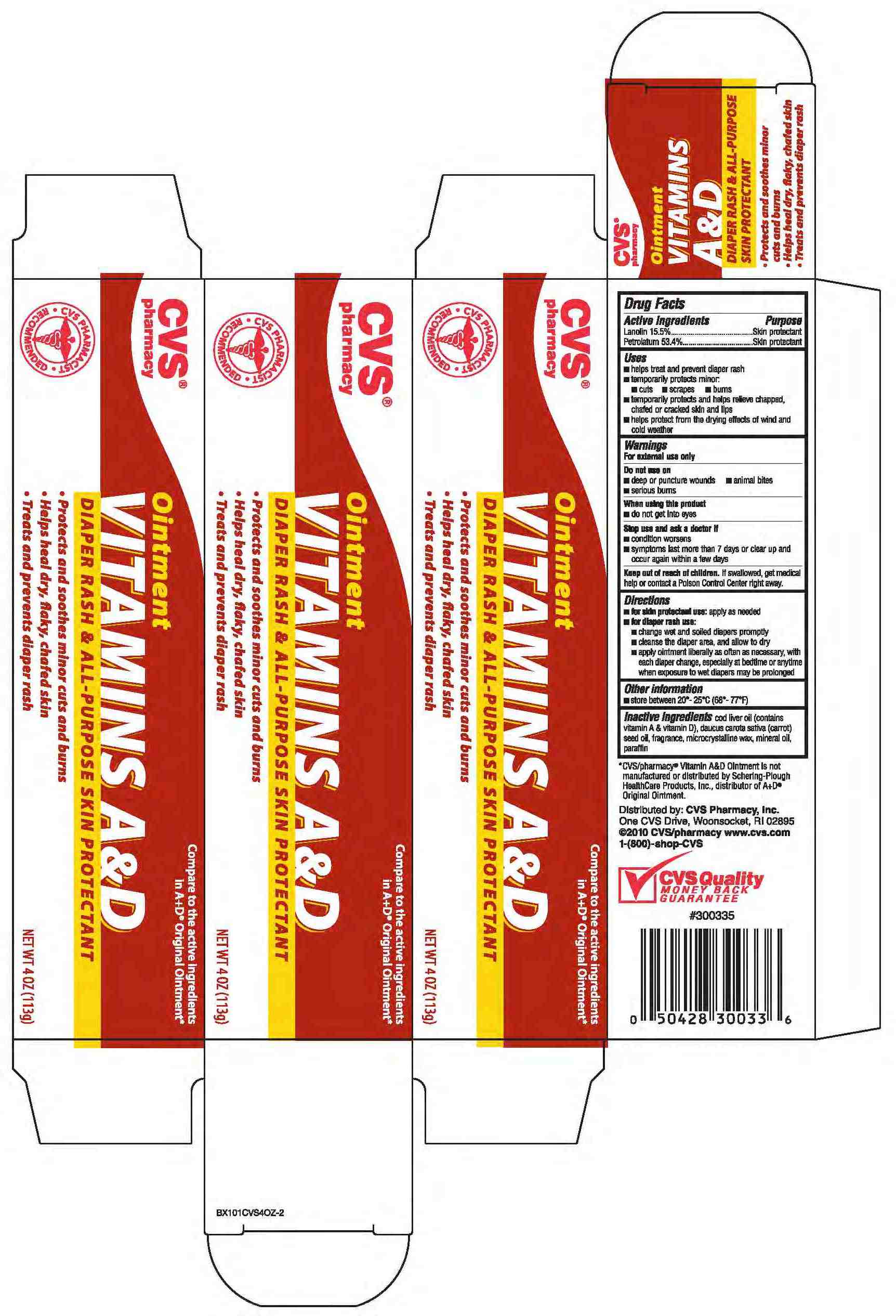 DRUG LABEL: PETROLATUM and LANOLIN
NDC: 59779-098 | Form: OINTMENT
Manufacturer: CVS
Category: otc | Type: HUMAN OTC DRUG LABEL
Date: 20110216

ACTIVE INGREDIENTS: PETROLATUM 534 mg/1 g; LANOLIN 155 mg/1 g
INACTIVE INGREDIENTS: PARAFFIN ; MICROCRYSTALLINE WAX; MINERAL OIL; COD LIVER OIL; CARROT SEED OIL

drug facts

Active ingredients Purpose
Lanolin 15.5%...................................Skin protectant
Petrolatum 53.4%.............................Skin protectant

Uses
- helps treat and prevent diaper rash
- temporarily protects minor:
- cuts - scrapes - burns
- temporarily protects and helps relieve chapped
chaffed or cracked skin and lips
- helps protect from the drying effects of wind and
cold weather

Keep out of reach of children. If swallowed, get medical
help or contact a Poison Control Center right away.

Uses
- helps treat and prevent diaper rash
- temporarily protects minor:
- cuts - scrapes - burns
- temporarily protects and helps relieve chapped
chaffed or cracked skin and lips
- helps protect from the drying effects of wind and
cold weather
Other information
- store between 20 degrees - 25 degrees C (68 degrees - 77 degrees F)

Warnings
For external use only.
_______________________________
Do not use on:
- deep or puncture wounds
- serious burns
_______________________________
When using this product
- do not get into the eyes
_______________________________
Stop use and ask a doctor if:
-condition worsens
-symptoms last more than 7 days or clear up and
occur again within a few days

Directions
-for skin protectional use: apply as needed
- for diaper rash use:
- change wet and soiled diapers promptly
- cleanse the diaper area and allow to dry
- apply ointment liberally as often as necessary, with
each diaper change, especially at bedtime or anytime
when exposure to wet diapers may be prolonged
- for other uses: apply as needed
________________________________
Other information
Store between 20 degrees to 25 degrees C (68 degrees to 77 degrees F)

Inactive Ingredients cod liver oil (contains
vitamin A and vitamin D), daucus carota sativa (carrot)
seed oil, fragrance, microcrystaling wax, mineral oil,
paraffin